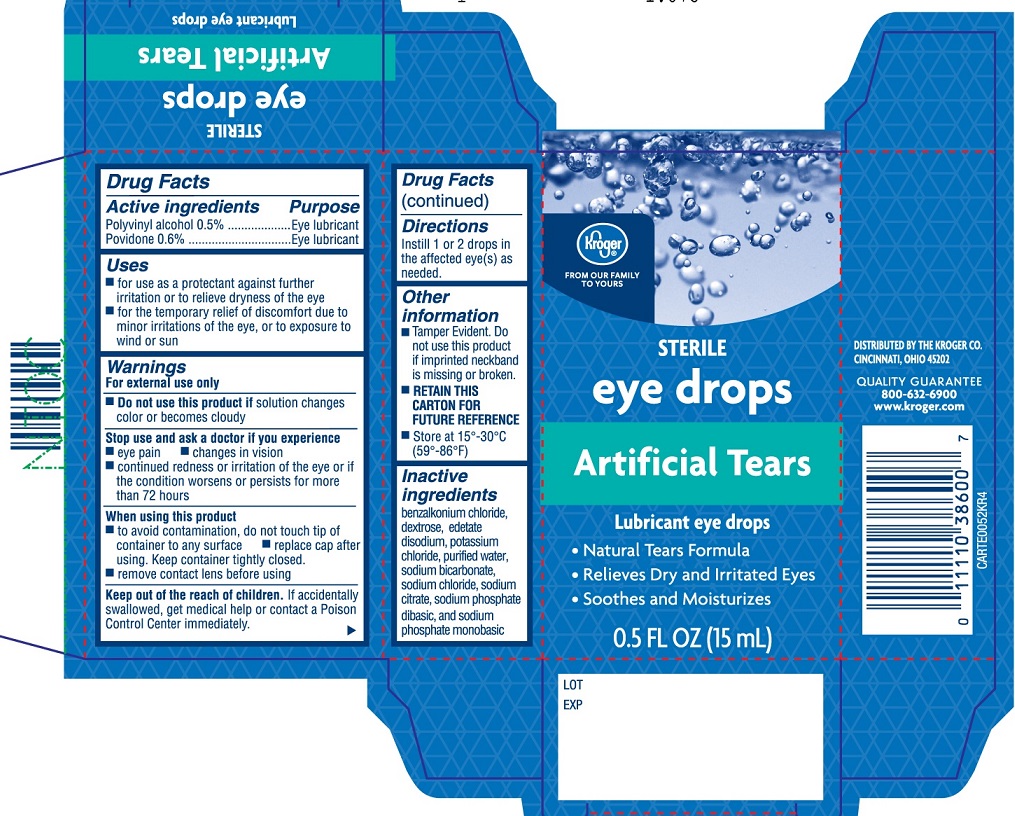 DRUG LABEL: Kroger Eye Drops Artificial Tears
NDC: 59450-814 | Form: SOLUTION/ DROPS
Manufacturer: The Kroger Company
Category: otc | Type: HUMAN OTC DRUG LABEL
Date: 20251230

ACTIVE INGREDIENTS: POVIDONE 0.6 g/100 mL; POLYVINYL ALCOHOL, UNSPECIFIED 0.5 g/100 mL
INACTIVE INGREDIENTS: POTASSIUM CHLORIDE; BENZALKONIUM CHLORIDE; EDETATE DISODIUM; WATER; SODIUM PHOSPHATE, MONOBASIC; SODIUM PHOSPHATE, DIBASIC; DEXTROSE; SODIUM BICARBONATE; SODIUM CHLORIDE; SODIUM CITRATE

Kroger Artificial Tears 15mL (PLD)

Active ingredients

Polyvinyl alcohol........0.5%

Povidone....................0.6%

Purpose

Polyvinyl alcohol............Eye lubricant

Povidone........................Eye lubricant

Uses

- for use as a protectant against further irritation or to relieve dryness of the eye
- for the temporary relief of discomfort due to minor irritations of the eye, or to exposure to wind or sun

Warnings

For external use only

Do not use this product if solution changes color or becomes cloudy

Stop use and ask a doctor if you experience

- eye pain
- changes in vision
- continued redness or irritation of the eye or if the condition worsens or persists for more than 72 hours

When using this product

- to avoid contamination, do not touch tip of container to any surface
- replace cap after using. Keep container tightly closed.
- remove contact lens before using

KEEP OUT OF REACH OF CHILDREN

Keep out of the reach of children. If accidentally swallowed, get medical help or contact a Poison Control Center immediately.

Directions

Instill 1 or 2 drops in the affected eye(s) as needed.

Other information

- Tamper Evident. Do not use this product if imprinted neckband is missing or broken.
- RETAIN THIS CARTON FOR FUTURE REFERENCE
- Store at 15º-30ºC (59º-86ºF)

Inactive ingredients

benzalkonium chloride, dextrose, edetate disodium, potassium chloride, purified water, sodium bicarbonate, sodium chloride, sodium citrate, sodium phosphate dibasic, and sodium phosphate monobasic